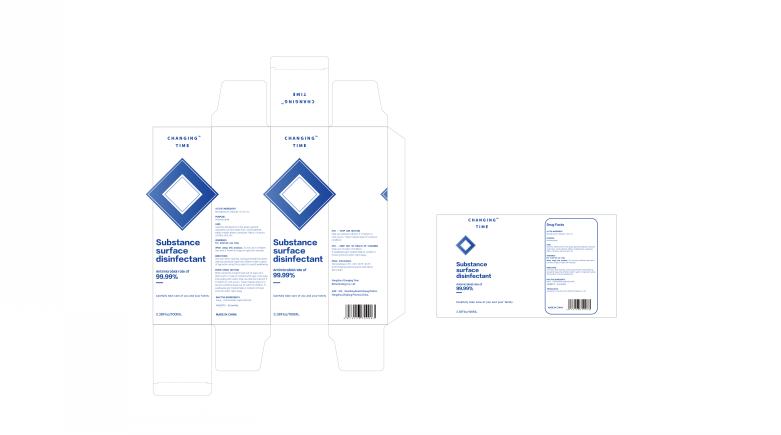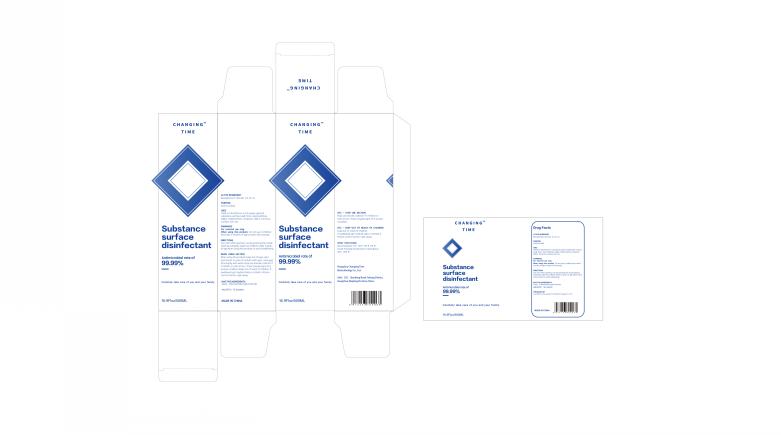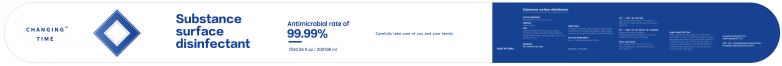 DRUG LABEL: Substance surface disinfectant
NDC: 75153-012 | Form: LIQUID
Manufacturer: Hangzhou Changing Time Biotechnology Co.,Ltd
Category: otc | Type: HUMAN OTC DRUG LABEL
Date: 20200630

ACTIVE INGREDIENTS: BENZALKONIUM CHLORIDE 0.2 g/100 mL
INACTIVE INGREDIENTS: WATER; POLIHEXANIDE HYDROCHLORIDE

Substance surface disinfectant

ACTIVE INGREDIENT

Benzalkonium chloride 0.2% v/v.

PURPOSE

Antimicrobial

USES

Used for disinfection in the space, general substance surface(wall,floor,stool, bathtub,table), mobile phone,computer, fabric,furniture,surface, skin, etc

WARNINGS

For external use only.

WHEN USING SECTION

When using this product keep out of eyes, ears, and mouth.In case of contact with eyes, rinse eyes thoroughly with water.Stop use and ask a doctor if irritation or rash occurs.These may be signs of a serious condition.Keep out of reach of children.If swallowed,

get medical help or contact a Poison Control Center right away.

Stop use and ask a doctor if irritation or rash occurs.These may be signs of a serious condition.

Keep out of reach of children.If swallowed,get medical help or contact a Poison Control Center right away.

DIRECTIONS

Use soon after opening.Use by pressing the nozzle placing outwards Supervise children under 6 years of age when using this product to avoid swallowing.

Other information

Store between 15℃-30℃(59°F-86°F)

Avoid freezing and excessive heat above 40C(104F)

INACTIVE INGREDIENTS

Aqua, Polihexanide Hydrochloride.